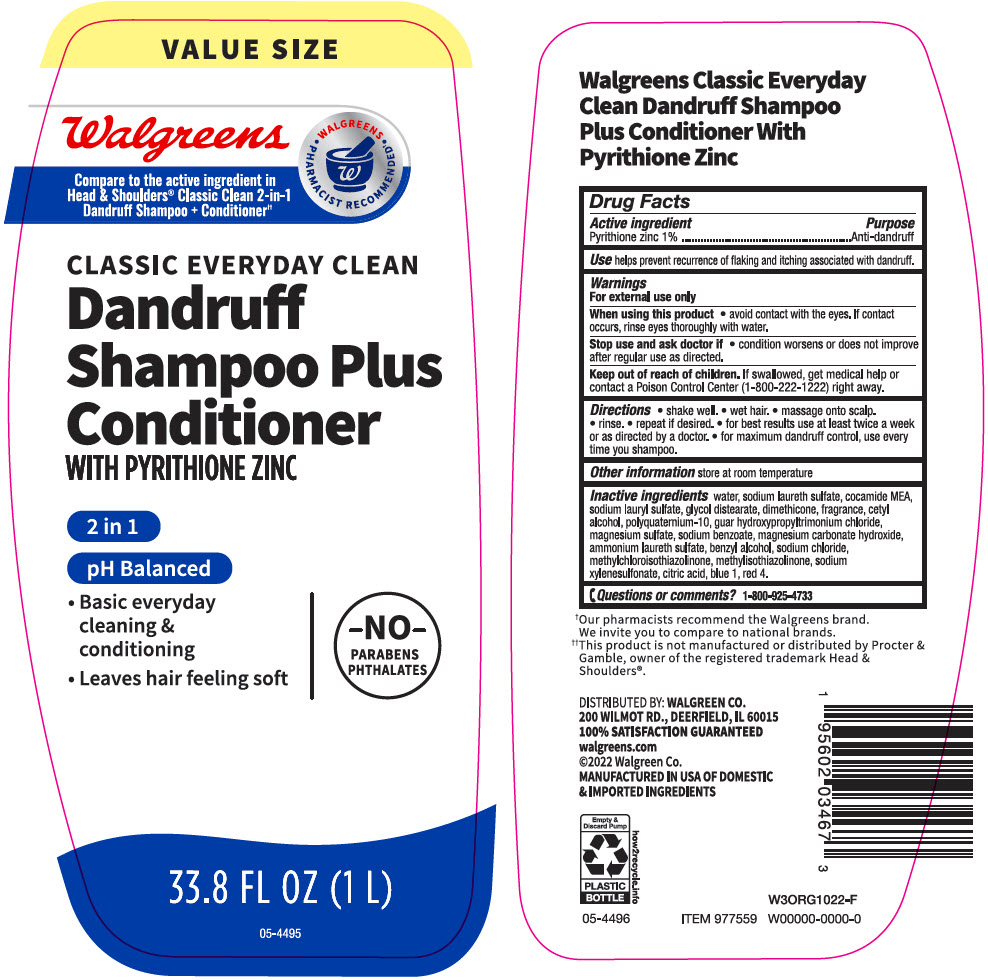 DRUG LABEL: Walgreens Dandruff Plus Conditioner 2 in 1
NDC: 0363-4673 | Form: SHAMPOO
Manufacturer: Walgreen Company
Category: otc | Type: HUMAN OTC DRUG LABEL
Date: 20241104

ACTIVE INGREDIENTS: Pyrithione Zinc 10 mg/1 mL
INACTIVE INGREDIENTS: Water; Sodium Laureth-3 Sulfate; Coco Monoethanolamide; Sodium Lauryl Sulfate; Glycol Distearate; Dimethicone; Cetyl Alcohol; Polyquaternium-10 (30000 MPA.S at 2%); GUAR HYDROXYPROPYLTRIMONIUM CHLORIDE; Magnesium Sulfate, Unspecified Form; Sodium Benzoate; Magnesium Carbonate Hydroxide; Ammonium Laureth-5 Sulfate; Benzyl Alcohol; Sodium Chloride; Methylchloroisothiazolinone; Methylisothiazolinone; Sodium Xylenesulfonate; Citric Acid Monohydrate; Fd&C Blue No. 1; Fd&C Red No. 4

Walgreens Dandruff Shampoo Plus Conditioner 2 in 1
Anti-dandruff

Drug Facts

Active ingredient

Pyrithione Zinc 1%

Purpose

Anti-dandruff

Use

helps prevent recurrence of flaking and itching associated with dandruff.

Warnings

For external use only

When using this product

- avoid contact with the eyes. If contact occurs, rinse eyes thoroughly with water.

Stop use and ask a doctor if

- condition worsens or does not improve after regular use as directed.

Keep out of reach of children. If swallowed, get medical help or contact a Poison Control Center (1-800-222-1222) right away.

Directions

- shake well
- wet hair
- massage onto scalp
- rinse
- repeat if desired
- for best results use at least twice a week or as directed by a doctor
- for maximum dandruff control, use every time you shampoo.

Other information

store at room temperature

Inactive ingredients

water, sodium laureth sulfate, cocamide MEA, sodium lauryl sulfate, glycol distearate, dimethicone, fragrance, cetyl alcohol, polyquaternium-10, guar hydroxypropyltrimonium chloride, magnesium sulfate, sodium benzoate, magnesium carbonate hydroxide, ammonium laureth sulfate, benzyl alcohol, sodium chloride, methylchloroisothiazolinone, methylisothiazolinone, sodium xylenesulfonate, citric acid, blue 1, red 4.

Questions or Comments?

1-800-925-4733

DISTRIBUTED BY: WALGREEN CO.
200 WILMOT RD., DEERFIELD, IL 60015

PRINCIPAL DISPLAY PANEL - 1 L Bottle Label

VALUE SIZE

Walgreens

Compare to the active ingredient in
Head & Shoulders® Classic Clean 2-in-1
Dandruff Shampoo + Conditioner††

• WALGREENS •
PHARMACIST RECOMMENDED†

CLASSIC EVERYDAY CLEAN
Dandruff
Shampoo Plus
Conditioner
WITH PYRITHIONE ZINC

2 in 1

pH Balanced

- Basic everyday
  cleaning &
  conditioning
- Leaves hair feeling soft

–NO–
PARABENS
PHTHALATES

33.8 FL OZ (1 L)

05-4495